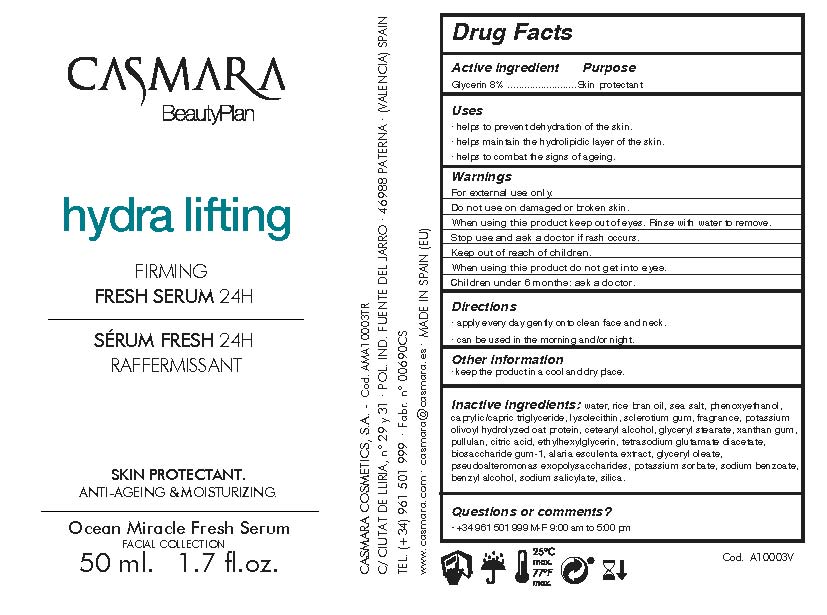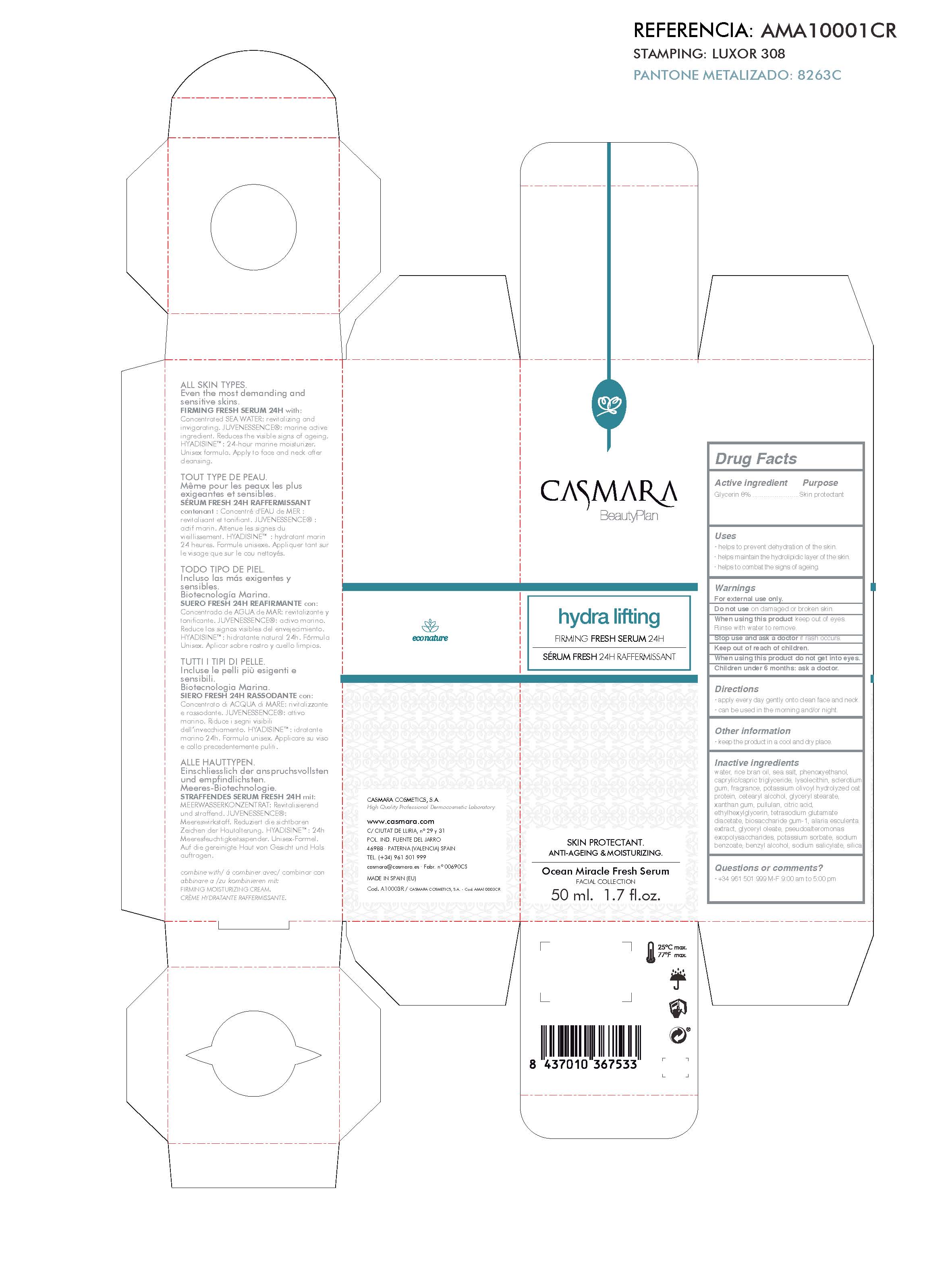 DRUG LABEL: Hydra Lifting Firming Fresh Serum 24H
NDC: 20151-093 | Form: CREAM
Manufacturer: CASMARA COSMETICS, SA
Category: otc | Type: HUMAN OTC DRUG LABEL
Date: 20170225

ACTIVE INGREDIENTS: GLYCERIN 8 mg/1 mL
INACTIVE INGREDIENTS: SODIUM BENZOATE 0.01 mg/1 mL; GLYCERYL OLEATE 0.05 mg/1 mL; BETASIZOFIRAN 0.35 mg/1 mL; POTASSIUM SORBATE 0.01 mg/1 mL; BENZYL ALCOHOL 0.01 mg/1 mL; SODIUM SALICYLATE 0.005 mg/1 mL; WATER 84.381 mg/1 mL; RICE BRAN OIL 2 mg/1 mL; SEA SALT 0.99 mg/1 mL; CETOSTEARYL ALCOHOL 0.3 mg/1 mL; GLYCERYL STEARATE SE 0.3 mg/1 mL; XANTHAN GUM 0.15 mg/1 mL; PULLULAN 0.15 mg/1 mL; CITRIC ACID MONOHYDRATE 0.1 mg/1 mL; ETHYLHEXYLGLYCERIN 0.1 mg/1 mL; TETRASODIUM GLUTAMATE DIACETATE 0.094 mg/1 mL; ALARIA ESCULENTA 0.05 mg/1 mL; PERFLUNAFENE 0.3 mg/1 mL; PHENOXYETHANOL 0.975 mg/1 mL; HYDROGENATED SOYBEAN LECITHIN 0.35 mg/1 mL; HYDROLYZED JOJOBA ESTERS (POTASSIUM SALTS) 0.3 mg/1 mL; SILICON DIOXIDE 0.0007 mg/1 mL; ALTEROMONAS MACLEODII 0.01 mg/1 mL; MEDIUM-CHAIN TRIGLYCERIDES 0.95 mg/1 mL

Hydra Lifting Firming Fresh Serum 24H

Active Ingredients Purpose

Glycerin 8%.................... Skin Protectant

Uses

. helps to prevent dehydration of the skin.

. helps maintain the hydrolipidic layer of the skin

. helps to combat the signs of ageing

Uses

. helps to prevent dehydration of the skin

. helps maintain the hydrolipidic layer of the skin

. helps to combat signs of ageing

Warnings

For external use only.

Do not use on damaged or broken skin.

When using this product keep our of the eyes. Rinse with water to remove.

Stop use and ask a doctor if rash occurs.

Keep out of reach of children.

Whhen using this product do not get into eyes.

Children under 6 months: as a doctor.

Keep out of reach of children.

Warnings

Stop use and ask a doctor if rash occurs.

Questions or comments?

(305) 777-0548 M-F 9:00 am to 5:00 pm

Directions

. apply every day gently onto clean face and neck.

. can be used in the morning and/or night.

Other information

. keep the product in a cool and dry place.

Inactive ingredients

Water, Rice bran oil, Sea salt, Phenoxyethanol, Caprylic/capric triglyceride, Lysolecithin, Sclerotium gum, Fragrance, Potassium olivoyl hydrolyzed oat protein, Cetearyl alcohol, Glyceryl stearate, Xanthan gum, Pullulan, Citric acid , Ethylhexylglycerin, Tetrasodium glutamate diacetate, Biosaccharide gum-1, Alaria esculenta extract, Glyceryl oleate, Pseudoalteromonas exopolysaccharides, Potassium sorbate, Sodium benzoate, Benzyl alcohol, Sodium salicylate, Silica

Directions

. apply every day gently onto clean face and neck

Firming FRESH SERUM 24H

Hydra lifting
Firming FRESH SERUM 24H
Skin Protectant
Anti-ageing & Moisturizing

Principal Display Panel

Hydralifting Firming Fresh Serum 24 hr

Skin Protectant

Anti-ageing-Moisturizing